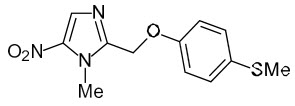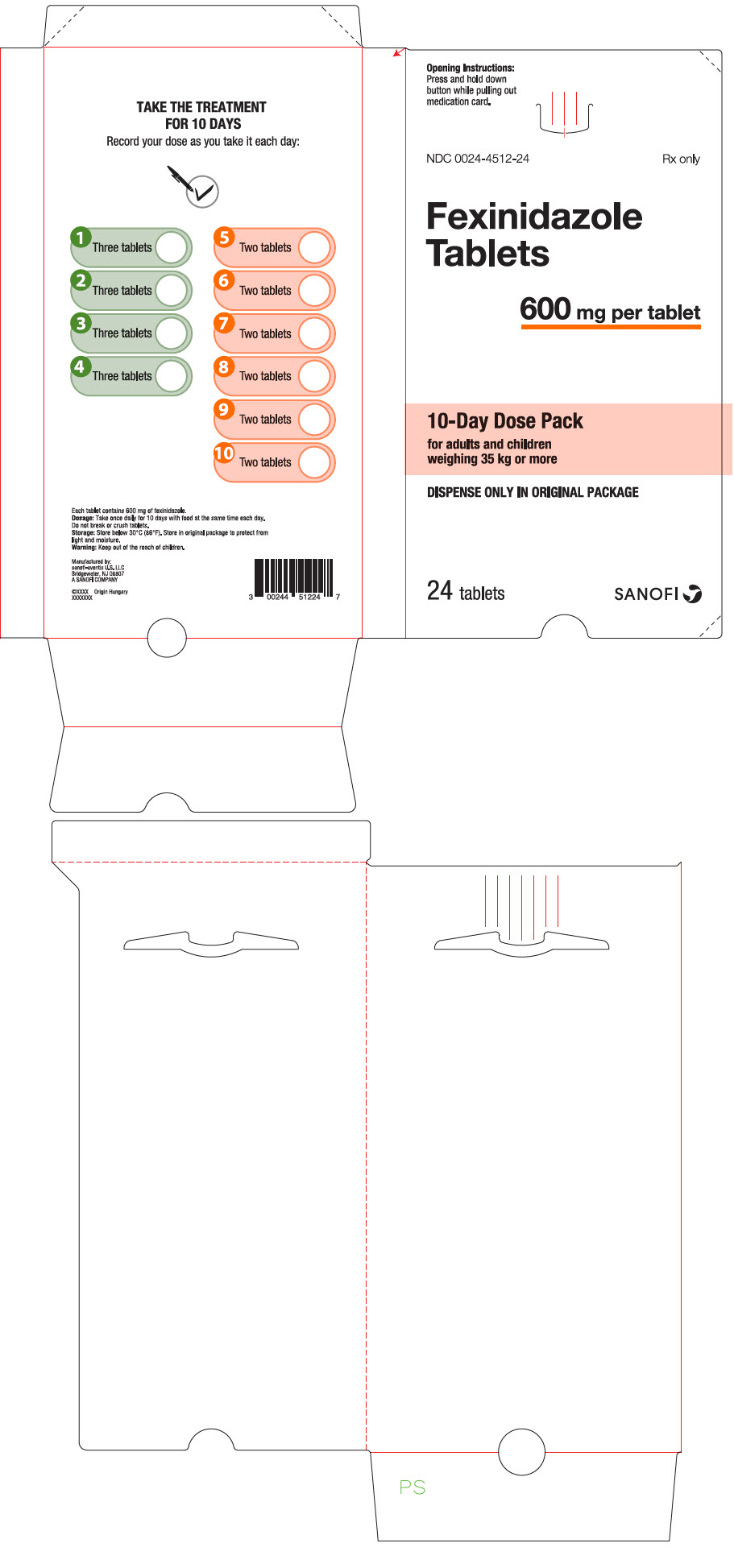 DRUG LABEL: Fexinidazole
NDC: 0024-4512 | Form: TABLET
Manufacturer: Sanofi-Aventis U.S. LLC
Category: prescription | Type: HUMAN PRESCRIPTION DRUG LABEL
Date: 20250502

ACTIVE INGREDIENTS: FEXINIDAZOLE 600 mg/1 1
INACTIVE INGREDIENTS: CROSCARMELLOSE SODIUM; LACTOSE MONOHYDRATE; MAGNESIUM STEARATE; MICROCRYSTALLINE CELLULOSE; POVIDONE, UNSPECIFIED; SODIUM LAURYL SULFATE

HIGHLIGHTS OF PRESCRIBING INFORMATION

These highlights do not include all the information needed to use FEXINIDAZOLE TABLETS safely and effectively. See full prescribing information for FEXINIDAZOLE TABLETS.
FEXINIDAZOLE tablets, for oral use
Initial U.S. Approval: 2021

RECENT MAJOR CHANGES

Contraindications (4) | 9/2024

1 INDICATIONS AND USAGE

Fexinidazole Tablets is a nitroimidazole antimicrobial, indicated for the treatment of both first-stage (hemolymphatic) and second-stage (meningoencephalitic) human African trypanosomiasis (HAT) due to Trypanosoma brucei gambiense in patients 6 years of age and older and weighing at least 20 kg. (1)

Limitations of Use

Due to the decreased efficacy observed in patients with severe second stage HAT (cerebrospinal fluid white blood cell count (CSF-WBC) >100 cells/µL) due to T. brucei gambiense disease, Fexinidazole Tablets should only be used in these patients if there are no other available treatment options. (1, 5.1)

2 DOSAGE AND ADMINISTRATION

Administer Fexinidazole Tablets once daily with food each day at about the same time of the day. Do not break or crush tablets. (2.1, 2.2)

Recommended Dosage of Fexinidazole Tablets in Patients 6 years of age and older and weighing at least 20 kg (2.2)
Body Weight | Type of Dose | Daily Dose | Number of Tablets | Duration of Treatment
Greater than or equal to 35 kg | Loading dose | 1,800 mg | 3 | 4 days
Greater than or equal to 35 kg | Maintenance dose | 1,200 mg | 2 | 6 days
Greater than or equal to 20 kg to less than 35 kg | Loading dose | 1,200 mg | 2 | 4 days
Greater than or equal to 20 kg to less than 35 kg | Maintenance dose | 600 mg | 1 | 6 days

3 DOSAGE FORMS AND STRENGTHS

Tablets: 600 mg (3)

4 CONTRAINDICATIONS

- Known hypersensitivity to fexinidazole, and/or nitroimidazole drugs (4)
- Patients with severe hepatic impairment (4)
- Patients with Cockayne syndrome (4)

5 WARNINGS AND PRECAUTIONS

- Decreased Efficacy in Severe Human African Trypanosomiasis caused by Trypanosoma brucei gambiense. (1, 5.1)
- QT Interval Prolongation: Prolongation of the QT interval due to Fexinidazole Tablets occurs in a concentration-dependent manner. Avoid use in patients with known prolongation, proarrhythmic conditions, and concomitant use with drugs that prolong the QT interval, those that block cardiac potassium channels, and/or those that induce bradycardia, or are inducers of hepatic CYP450. (5.2, 7.1, 7.2, 12.2)
- Neuropsychiatric Adverse Reactions: Adverse reactions such as agitation, anxiety, abnormal behavior, depression, suicidal ideation, nightmares, hallucination, and personality change have been observed during therapy. Inform patients and their caregivers of the risk. Consider alternative therapy or increased monitoring of the patient, including hospitalization in patients with psychiatric disorders, or if these adverse reactions occur. (5.3)
- Neutropenia: Avoid concomitant use of drugs which may cause neutropenia and monitor leukocyte count periodically. Monitor patients with neutropenia for symptoms or signs of infection. (5.4, 6.1)
- Potential for Hepatotoxicity: Evaluate liver-related laboratory tests at the start and during treatment. (4, 5.5)
- Risk of Disulfiram-like Reactions Due to Concomitant Use with Alcohol: Nitroimidazole-class drugs may cause a disulfiram-like reaction in patients who concurrently consume alcohol. Advise patients to avoid consumption of alcohol during treatment with and for at least 48 hours after completing therapy. (2.1, 5.6)
- Risk of Psychotic Reactions Due to Concomitant Use with Disulfiram: Psychotic reactions have been reported in patients concurrently taking disulfiram and nitroimidazole-class drugs. Avoid use in patients who have taken disulfiram within the last two weeks. (5.7).

6 ADVERSE REACTIONS

Most common adverse reactions (incidence >10%) are headache, vomiting, insomnia, nausea, asthenia, tremor, decreased appetite, dizziness, hypocalcemia, dyspepsia, back pain, upper abdominal pain, and hyperkalemia. (6.1)

To report SUSPECTED ADVERSE REACTIONS, contact sanofi-aventis U.S. LLC at 1-800-633-1610 or FDA at 1-800-FDA-1088 or www.fda.gov/medwatch.

7 DRUG INTERACTIONS

- Avoid use of herbal medicines and supplements. (7.1)
- See full prescribing information for complete list of clinically significant drug interactions. (7.2)

8 USE IN SPECIFIC POPULATIONS

- Avoid use in patients with severe renal impairment. (8.6)

FULL PRESCRIBING INFORMATION

1 INDICATIONS AND USAGE

Fexinidazole Tablets are indicated for the treatment of both the first-stage (hemolymphatic) and second-stage (meningoencephalitic) human African trypanosomiasis (HAT) due to Trypanosoma brucei gambiense in patients 6 years of age and older and weighing at least 20 kg.

Limitations of Use

Due to the decreased efficacy observed in patients with severe second stage HAT (cerebrospinal fluid white blood cell count (CSF-WBC) >100 cells/µL) due to T. brucei gambiense disease, Fexinidazole Tablets should only be used in these patients if there are no other available treatment options [see Warnings and Precautions (5.1)].

2 DOSAGE AND ADMINISTRATION

2.1 Important Administration Instructions

- Patients should be closely followed by their healthcare provider during treatment with Fexinidazole Tablets.
- Fexinidazole Tablets must be administered with food [see Dosage and Administration (2.2)].
- Avoid consumption of alcoholic beverages during treatment with Fexinidazole Tablets and for at least 48 hours after completing therapy [see Warnings and Precautions (5.6)].
- If a first event of vomiting occurs after receiving Fexinidazole Tablets, do not re-dose. Administer the next dose the following day using the recommended treatment schedule [see Adverse Reactions (6.1)].
- If a scheduled dose is missed (not taken on the assigned day), normal dosing should resume the following day until the full course (10 days) of treatment has been completed. The clinical consequences of multiple missed doses of Fexinidazole Tablets are not known.

2.2 Recommended Dosage

Administer Fexinidazole Tablets, orally, once daily for a total of 10 days (loading dose plus maintenance dose) with food each day at about the same time of the day. Do not break or crush Fexinidazole Tablets.

The recommended dosage of Fexinidazole Tablets for patients 6 years of age and older is according to body weight as described in Table 1 below.

Table 1: Recommended Dosage of Fexinidazole Tablets in Patients 6 Years of Age and Older and Weighing at Least 20 kg
Body weight | Type of Dose | Recommended [Administer Fexinidazole Tablets once daily with food each day at about the same time of the day] Daily Dose | Number of 600 mg Fexinidazole Tablets Daily | Duration of Treatment
Greater than or equal to 35 kg | Loading dose | 1,800 mg | 3 | 4 days
Greater than or equal to 35 kg | Maintenance dose | 1,200 mg | 2 | 6 days
Greater than or equal to 20 kg to less than 35 kg | Loading dose | 1,200 mg | 2 | 4 days
Greater than or equal to 20 kg to less than 35 kg | Maintenance dose | 600 mg | 1 | 6 days

3 DOSAGE FORMS AND STRENGTHS

Tablets: 600 mg of fexinidazole per tablet as pale-yellow, round, biconvex tablets debossed with "4512" on one side.

4 CONTRAINDICATIONS

Fexinidazole Tablets are contraindicated in:

- Patients with known hypersensitivity to Fexinidazole Tablets and/or any nitroimidazole-class drugs (e.g., metronidazole, tinidazole).
- Patients with severe hepatic impairment [see Warnings and Precautions (5.5), Adverse Reactions (6.1), and Use in Specific Populations (8.7)].
- Patients with Cockayne syndrome. Severe irreversible hepatotoxicity/acute liver failure with fatal outcomes have been reported after initiation of metronidazole, another nitroimidazole drug, structurally related to fexinidazole, in patients with Cockayne syndrome [see Adverse Reactions (6.2)].

5 WARNINGS AND PRECAUTIONS

5.1 Decreased Efficacy in Severe Human African Trypanosomiasis Caused by Trypanosoma brucei gambiense

Decreased efficacy was observed in patients treated with Fexinidazole Tablets as compared to nifurtimox-eflornithine combination therapy (NECT)-treated patients in a randomized, comparative open-label study in the subgroup of patients with severe second stage disease, as defined by cerebrospinal fluid white blood cell count (CSF-WBC) >100 cells/µL at baseline [see Clinical Studies (14)]. The 18-month success rate in this subgroup of patients with severe second stage disease was 86.9% with Fexinidazole Tablets compared to 98.7% with NECT with a difference of -11.8%, 95% confidence interval (CI) (-18.3%, -2.1%). All-cause mortality was higher in patients with severe disease treated with Fexinidazole Tablets than in patients treated with NECT through 24 months (7/160 [4.4%] vs 0/78 [0%], treatment difference 4.4%, 95% CI [-0.9%, 8.9%]).

Patients with severe second stage HAT (CSF-WBC >100 cells/µL) due to T. brucei gambiense disease should only be treated with Fexinidazole Tablets if there are no other available treatment options.

5.2 QT Interval Prolongation

Fexinidazole Tablets have been shown to prolong the QT interval in a concentration-dependent manner [see Clinical Pharmacology (12.2)]. Treatment with Fexinidazole Tablets caused an average increase of 19 msec in the QTcF interval. In clinical trials in HAT patients, three (<1%) patients in the fexinidazole group had a QTcF value of >500 ms versus none in the nifurtimox-eflornithine combination therapy (NECT) group.

Avoid use of Fexinidazole Tablets in patients who have:

- QTcF interval greater than 470 msec
- A history of torsade de pointes, congenital long QT syndrome, cardiac arrhythmias, uncompensated heart failure, or family history of sudden death
- Uncorrected hypokalemia

Avoid concomitant administration of Fexinidazole Tablets with other drugs that are known to prolong the QT interval, those that block cardiac potassium channels, and/or those that induce bradycardia [see Drug Interactions (7.1)].

Avoid concomitant administration of Fexinidazole Tablets with drugs that are inducers of hepatic CYP450 as these drugs may significantly increase plasma concentrations of fexinidazole's active metabolites: fexinidazole sulfoxide (M1) and fexinidazole sulfone (M2). M2 plasma concentrations have been associated with increased QT prolongation risks [see Drug Interactions (7.2)].

If patients are, or need to be, treated with drugs known to prolong QTcF interval or to induce bradycardia either do not initiate therapy with Fexinidazole Tablets until such drugs are eliminated from the body (allow a washout period of 5 half-lives for such other drugs), or do not start such drugs until fexinidazole is eliminated from the body (allow a washout period of 7 days for Fexinidazole Tablets).

5.3 Neuropsychiatric Adverse Reactions

Adult patients treated with Fexinidazole Tablets reported a higher percentage of Central Nervous System (CNS) and psychiatric-related adverse reactions than those treated with nifurtimox eflornithine combination therapy (NECT) in a clinical trial [see Adverse Reactions (6.1)]. Increased incidence in insomnia, headache, and tremor was noted in the patients treated with Fexinidazole Tablets compared to NECT. In the same trial, adverse reactions representing mood changes and psychiatric disorders (such as agitation, anxiety, abnormal behavior, depression, nightmares, hallucination, and personality change) were more common in the patients treated with Fexinidazole Tablets compared to the NECT arm. Suicidal ideation has also been observed with Fexinidazole Tablets [see Adverse Reactions (6.1)]. Healthcare providers should inform patients and their caregivers of the risk for neuropsychiatric adverse reactions during treatment with Fexinidazole Tablets. In patients with current or a history of psychiatric disorders, or should such adverse reactions occur, healthcare providers should consider alternative therapy or increased monitoring of the patient, including hospitalization.

5.4 Neutropenia

Neutropenia (absolute neutrophil count less than 1,000 cells/mm^3) has been reported in patients receiving Fexinidazole Tablets [see Adverse Reactions (6.1)]. In Trial 1, the adverse reaction occurred in patients with a baseline absolute neutrophil count of less than 5,000 cells/mm^3. Avoid concomitant use of drugs which may cause neutropenia and monitor leukocyte count periodically. Carefully monitor patients with neutropenia for fever or other symptoms or signs of infection and treat promptly if such symptoms or signs occur.

5.5 Potential for Hepatotoxicity

Elevations in liver transaminases occurred in less than two percent of patients receiving Fexinidazole Tablets for the treatment of HAT [see Adverse reactions (6.1) and Overdosage (10)]. Evaluate liver-related laboratory tests at the start [see Contraindications (4)] and during treatment with Fexinidazole Tablets. Monitor patients who develop abnormal liver-related laboratory tests during treatment with Fexinidazole Tablets.

5.6 Risk of Disulfiram-like Reaction Due to Concomitant Use with Alcohol

Nitroimidazole-class drugs may cause a disulfiram-like reaction characterized by flushing, rash, weakness, abdominal cramps, nausea, vomiting and headache in patients who concurrently consume alcohol. Advise patients to avoid consumption of alcohol during treatment with Fexinidazole Tablets and for at least 48 hours after completing therapy [see Dosage and Administration (2.1)].

5.7 Risk of Psychotic Reactions Due to Concomitant Use with Disulfiram

Psychotic reactions have been reported in patients who were concurrently taking disulfiram and nitroimidazole drugs. Avoid use of Fexinidazole Tablets in patients who have taken disulfiram within the last two weeks.

6 ADVERSE REACTIONS

The following serious and otherwise important adverse reactions are discussed in greater detail in other sections of labeling:

- Decreased Efficacy in Severe Human African Trypanosomiasis Caused by Trypanosoma brucei gambiense [see Warnings and Precautions (5.1)]
- QT Interval Prolongation [see Warnings and Precautions (5.2)]
- Neuropsychiatric Adverse Reactions [see Warnings and Precautions (5.3)]
- Neutropenia [see Warnings and Precautions (5.4)]
- Potential for Hepatotoxicity [see Warnings and Precautions (5.5)]

6.1 Clinical Trials Experience

Because clinical trials are conducted under widely varying conditions, adverse reaction rates observed in the clinical trials of a drug cannot be directly compared to rates in the clinical trials of another drug and may not reflect the rates observed in practice.

Fexinidazole Tablets were evaluated for the treatment of HAT due to T. brucei gambiense in three clinical trials, of which one was comparative and two were noncomparative. Trial 1 compared the safety of Fexinidazole Tablets to nifurtimox-eflornithine combination therapy (NECT) in second stage, meningoencephalitic HAT (N=394). Trial 2 enrolled patients with stage 1 hemolymphatic and early stage 2 HAT (N=230), and Trial 3 assessed the safety of fexinidazole in pediatric patients aged 6 years or older with any stage HAT (N=125).

The three trials were primarily conducted in the Democratic Republic of Congo (DRC) and a total of 749 patients received at least one dose of study medication. The patients ranged from 6 to 73 years of age, and 11 were more than 65 years old. Trials 1 and 3 enrolled more males than females (61% and 54% were males, respectively), while the gender distribution was equally balanced in Trial 2. The mean BMI ranged from 16.1 to 19.3 kg/m^2 across trials which was consistent with the nutritional status of the study population. Patients with AST/ALT >2 times the upper limit of normal or total bilirubin >1.5 the upper limit of normal were excluded from the trials.

Trial 1 included 264 patients in the fexinidazole treatment arm and 130 patients in the NECT treatment arm. The patients were followed for up to 24 months from the completion of treatment.

Common Adverse Reactions

The most common adverse reactions occurring in >10% of HAT patients (15 years of age and older) receiving Fexinidazole Tablets in Trial 1 were headache, vomiting, insomnia, nausea, asthenia, tremor, decreased appetite, dizziness, hypocalcemia, dyspepsia, back pain, upper abdominal pain, and hyperkalemia.

Selected adverse reactions occurring in ≥2% of HAT patients 15 years of age and older receiving Fexinidazole Tablets in Trial 1 are provided in Table 2.

Table 2: Selected Adverse Reactions Occurring in ≥2% of HAT Patients 15 Years of Age and Older Receiving Fexinidazole Tablets in Trial 1
Adverse Reaction | Fexinidazole Tablets N=264 N (%) | NECT N=130 N (%)
Blood and lymphatic system disorders
Neutropenia [Defined as an absolute neutrophil count of less than 1,000 cells/mm^3 occurring at any time following the first dose of study drug to the end of the study.] | 15 (5.7%) | 4 (3.1%)
Cardiac disorders
Palpitations | 13 (4.9%) | 5 (3.8%)
Eye disorders
Photophobia | 6 (2.3%) | 0
Gastrointestinal disorders
Vomiting | 75 (28.4%) | 37 (28.4%)
Nausea | 68 (25.8%) | 20 (15.4%)
Dyspepsia | 34 (12.9%) | 10 (7.7%)
Abdominal pain upper | 27 (10.2%) | 6 (4.6%)
Salivary hypersecretion | 16 (6.1%) | 3 (2.3%)
Constipation | 13 (4.9%) | 2 (1.5%)
Abdominal distension | 8 (3.0%) | 0
Gastritis | 8 (3.0%) | 2 (1.5%)
General disorders and administration site conditions
Asthenia | 60 (22.7%) | 19 (14.6%)
Feeling hot | 25 (9.5%) | 3 (2.3%)
Chest pain | 23 (8.7%) | 5 (3.8%)
Gait disturbance | 12 (4.5%) | 2 (1.5%)
Metabolism and nutrition disorders
Decreased appetite | 56 (21.2%) | 24 (18.5%)
Hypocalcemia | 36 (13.6%) | 3 (2.3%)
Hypoalbuminemia | 23 (8.7%) | 4 (3.1%)
Musculoskeletal and connective tissue disorders
Back pain | 30 (11.4%) | 12 (9.2%)
Neck pain | 23 (8.7%) | 7 (5.4%)
Muscle Spasms | 7 (2.7%) | 1 (0.8%)
Nervous system disorders
Headache | 92 (34.8%) | 32 (24.6%)
Tremor | 58 (22.0%) | 15 (11.5%)
Dizziness | 50 (18.9%) | 18 (13.8%)
Extrapyramidal disorder | 9 (3.4%) | 2 (1.5%)
Paresthesia | 6 (2.3%) | 0
Psychiatric disorders
Insomnia | 74 (28.0%) | 15 (11.5%)
Agitation | 10 (3.8%) | 1 (0.8%)
Anxiety | 10 (3.8%) | 0
Abnormal behavior | 7 (2.7%) | 1 (0.8%)
Respiratory, thoracic and mediastinal disorders
Cough | 16 (6.0%) | 6 (4.6%)
Dyspnea | 6 (2.3%) | 1 (0.8%)
Skin and subcutaneous tissue disorders
Pruritus | 10 (3.8%) | 4 (3.1%)
Hyperhidrosis | 7 (2.7%) | 2 (1.5%)
Vascular disorders
Hot flush | 13 (4.9%) | 4 (3.1%)
Hypertension | 12 (4.5%) | 1 (0.8%)

Other Adverse Reactions with Fexinidazole Tablets Occurring in Trial 1

The following adverse reactions were reported in less than 2% of patients aged 15 years and older with HAT, treated with Fexinidazole Tablets in Trial 1:

Psychiatric Disorders: hallucinations, psychotic disorder, depression, personality change, suicidal ideation

Laboratory Investigations: elevations of liver transaminases [see Warnings and Precautions (5.5)] and Overdosage (10)]

The safety profile of Fexinidazole Tablets in Trials 2 and 3, including in pediatric subjects aged 6–15 years old, was similar to that of Trial 1 [see Use in Specific Populations (8.4)].

Specific Adverse Reactions

Vomiting

In the clinical trials, the incidence of vomiting within 30 minutes of administration of Fexinidazole Tablets was higher in pediatric patients (20%) than in adult patients (6.1%). There was a trend of increased incidence of vomiting during the loading phase. Generally, vomiting did not lead to treatment discontinuation.

6.2 Postmarketing Experience

The following adverse reaction has been identified and reported during post-approval use of other nitroimidazole agents. Because the reports of this reaction are voluntary and the population is of uncertain size, it is not always possible to reliably estimate the frequency of the reaction or establish a causal relationship to drug exposure.

Metronidazole, Another Nitroimidazole Product, Structurally Related to Fexinidazole: Cases of severe irreversible hepatotoxicity/acute liver failure, including cases with fatal outcomes with very rapid onset after initiation of systemic use of metronidazole, another nitroimidazole agent structurally related to fexinidazole, have been reported in patients with Cockayne syndrome (latency from drug start to signs of liver failure as short as 2 days) [see Contraindications (4)].

7 DRUG INTERACTIONS

7.1 Pharmacodynamic Interactions

Herbal Medicines and Supplements

There is a potential for pharmacodynamic interactions and/or toxicities between fexinidazole and herbal medicines and supplements. Avoid concomitant use of herbal medicines and supplements during treatment with Fexinidazole Tablets.

Drugs that May Prolong the QT Interval and/or Induce Bradycardia

Coadministration of Fexinidazole Tablets with drugs known to block potassium channels (e.g., antiarrhythmics, neuroleptics, fluoroquinolones, imidazole and triazole antifungals, pentamidine) prolong the QT interval (e.g., antimalarials, phenothiazines, tricyclic antidepressants, terfenadine and astemizole, IV erythromycin, and quinolone antibacterial drugs) and/or induce bradycardia (such as β-blockers) should be avoided [see Warnings and Precautions (5.2)].

7.2 Pharmacokinetic Drug Interactions

Table 3: Effect of Fexinidazole on other Drugs
Drugs Metabolized by Cytochrome P450 (CYP) 3A4/5
Examples (not fully inclusive): | Lovastatin, simvastatin, nisoldipine, saquinavir, midazolam, certain hormonal contraceptives (e.g., birth control pills, skin patches, implant)
Clinical Impact | Fexinidazole is considered a moderate CYP3A4/5 inducer [see Clinical Pharmacology (12.3)]. Co-administration of Fexinidazole Tablets and CYP3A4/5 substrates may reduce the systemic exposures of CYP3A4/5 substrate drug(s), which may lead to reduced efficacy [see Clinical Pharmacology (12.3)].
Prevention or Management | Avoid concomitant use with Fexinidazole Tablets. If coadministration cannot be avoided, monitor for lack of efficacy of sensitive substrate drugs. If concomitant use of oral contraceptives cannot be avoided, an alternative contraceptive that is not affected by enzyme inducers (e.g., intrauterine system) or additional nonhormonal contraception (e.g., condoms) is recommended during treatment with Fexinidazole Tablets and for at least 5 days after the last dose.
Drugs Metabolized by CYP1A2 or CYP2C19
Examples (not fully inclusive): | CYP1A2: duloxetine, tacrine, tizanidine, theophylline CYP2C19: lansoprazole, mephenytoin, diazepam
Clinical Impact | Increased risk for adverse reactions associated with increased concentrations of the drug due to inhibition of either CYP1A2 or CYP2C19 by fexinidazole [see Clinical Pharmacology (12.3)].
Prevention or Management | Monitor for adverse reactions associated with these drugs when used concomitantly with Fexinidazole Tablets.
Drugs Metabolized by CYP2B6
Examples (not fully inclusive): | Bupropion, efavirenz
Clinical Impact | Increased risk for the lack of efficacy associated with decreased plasma concentrations of the drug due to induction of CYP2B6 by fexinidazole and Metabolite M1 [see Clinical Pharmacology (12.3)].
Prevention or Management | Avoid concomitant use with Fexinidazole Tablets. If coadministration cannot be avoided, monitor for lack of efficacy of these drugs.
Drugs Metabolized by uridine 5'-diphospho--glucuronosyl transferase (UGT)
Examples (not fully inclusive): | Zidovudine, bictegravir, cabotegravir, dolutegravir, bexagliflozin, canagliflozin, sotagliflozin, deferasirox, lamotrigine, selexipag
Clinical Impact | Fexinidazole metabolites have the potential to be UGT inducers [see Clinical Pharmacology (12.3)]. Co-administration of Fexinidazole Tablets and UGT substrates may reduce the systemic exposures of UGT substrate drug(s), which may lead to reduced efficacy.
Prevention or Management | When fexinidazole is concomitantly administered with UGT substrates, monitor for lack of efficacy of UGT substrate drugs.
Drugs Substrates of OCT2, OAT1, OAT3, MATE1, and MATE2-K Transporters
Examples (not fully inclusive): | Metformin, dofetilide, adefovir, cefaclor, furosemide
Clinical Impact | Increased risk for adverse reactions associated with increased concentrations of the drug due to inhibition of these transporters by fexinidazole [see Clinical Pharmacology (12.3)].
Prevention or Management | Avoid concomitant use with Fexinidazole Tablets. If coadministration cannot be avoided, monitor for adverse reactions associated with these drugs.

Table 4: Effect of other Drugs on Fexinidazole
CYP450 Inducers
Examples (not fully inclusive): | Rifampin, phenytoin, St. John's wort, carbamazepine
Clinical Impact | Increased risk for adverse reactions associated with increased systemic exposure to the M1 and M2 metabolites of fexinidazole. M2 plasma concentrations have been associated with the increased risk of QT interval prolongation.
Prevention or Management | Avoid concomitant use with Fexinidazole Tablets [see Warnings and Precautions (5.2) and Clinical Pharmacology (12.3)].
CYP450 Inhibitors
Examples (not fully inclusive): | Clarithromycin, itraconazole, voriconazole, erythromycin, fluconazole
Clinical Impact | Multiple CYP450 enzymes are involved in the metabolism of fexinidazole to its pharmacologically active M1 and M2 metabolites. Although no clinical drug interaction studies were performed with CYP450 inhibitors, the formation of the M1 and M2 metabolites may be decreased.
Prevention or Management | Avoid concomitant use with Fexinidazole Tablets. If coadministration cannot be avoided, monitor for lack of efficacy of fexinidazole due to potential for decreased plasma concentrations of the M1 and M2 metabolites [see Clinical Pharmacology (12.3)].

8 USE IN SPECIFIC POPULATIONS

8.1 Pregnancy

Risk Summary

There are risks to the mother and fetus associated with untreated HAT due to T. brucei gambiense during pregnancy (see Clinical Considerations). Available data from clinical trials with fexinidazole use in pregnant women are insufficient to evaluate for a drug-associated risk of major birth defects or miscarriage.

There were no effects on prenatal development in embryo-fetal studies where pregnant rats were administered oral fexinidazole during organogenesis at a dose similar to the clinical dose based on AUC comparisons. Effects of fexinidazole on embryo-fetal development were observed in the rat and in the rabbit at doses harmful to the dams only. Exposure of fexinidazole and its metabolites at those maternal toxic doses in rats and rabbits were 2 times and less than 0.02 times the clinical exposure, respectively. In the prenatal and postnatal development study, administration of oral fexinidazole to pregnant rats during organogenesis and through lactation resulted in lower body weights in first generation offspring from dams treated at approximately 1.03 times the clinical exposure based on AUC comparisons.

The estimated background risk of major birth defects and miscarriage for the indicated population is unknown. All pregnancies have a background risk of birth defect, loss or other adverse outcomes. In the U.S. general population, the estimated background risk of major birth defects and miscarriage in clinically recognized pregnancies is 2% to 4% and 15% to 20%, respectively.

Clinical Considerations

Disease-associated maternal and/or embryo/fetal Risk

There are adverse effects on maternal and fetal outcomes associated with untreated HAT due to T. brucei gambiense in pregnancy. Disease progression may occur during pregnancy. Pregnant women should be treated for HAT due to T. brucei gambiense during pregnancy to prevent vertical transmission. For timing of treatment during pregnancy, consider the benefits of Fexinidazole Tablets to the mother and the potential risks to the fetus.

Data

Animal data

In the embryo-fetal toxicity studies, pregnant rats were exposed from gestation day (GD) 6 through GD 17. There was no effect on prenatal development in the rat up to the daily dose of 200 mg/kg, similar to the clinical dose based on AUC comparisons.

Maternal toxicity was evidenced by the significantly reduced body weight gain observed at 800 mg/kg. Delayed ossification (sternebrae, metacarpals and caudal vertebrae) and reduced fetal and placental weights were observed in the presence of maternal toxicity.

In the rabbit embryo-fetal development study, pregnant rabbits were exposed from GD 6 to GD 20. Fexinidazole resulted in abortions in the presence of maternal toxicity (reduced food consumption and reduced body weight gain) at doses of 20 mg/kg/day and above, less than 0.02 times the clinical exposures, based on pharmacokinetics comparisons.

In the prenatal and postnatal development study, female rats were exposed from GD 6 to lactation day 21. Lower body weights were reported in F1 pups from dams treated (approximately 1.03 times the clinical exposure based on AUC comparisons) throughout lactation. Sexual maturity showed a minimal delay for both males and females. Postweaning development for behavior and reproductive performance did not indicate any late adverse effect on the progeny.

8.2 Lactation

Risk Summary

There are no data on the presence of fexinidazole in human milk or the effect on milk production. There are no reports of adverse effects to the breastfed child associated with fexinidazole exposure through breastmilk based on a limited number of reported cases. Fexinidazole is present in rat milk (see Data). When a drug is present in animal milk, it is likely that the drug will be present in human milk.

The developmental and health benefits of breastfeeding should be considered along with the mother's clinical need for Fexinidazole Tablets and any potential adverse effects on the breastfed child from fexinidazole or from the underlying maternal condition.

Data

In lactating rats given a single oral dose of 800 mg/kg 14C-fexinidazole, fexinidazole and/or related metabolites were detected in the milk.

8.4 Pediatric Use

The safety and effectiveness of Fexinidazole Tablets for the treatment of both the first-stage (hemolymphatic) and second-stage (meningoencephalitic) HAT due to Trypanosoma brucei gambiense have been established in pediatric patients aged 6 years and older and weighing at least 20 kg. Use of Fexinidazole Tablets for this indication is supported by evidence from an adequate and well-controlled trial in adults with additional efficacy, pharmacokinetic and safety data in pediatric patients aged 6 years and older [see Adverse Reactions (6.1), Clinical Pharmacology (12.3), and Clinical Studies (14)].

Pediatric patients may be more sensitive to vomiting. The safety profile for Fexinidazole Tablets in pediatric patients was generally similar to that of adult patients with the exception of more frequent vomiting within 2 hours of administration of Fexinidazole Tablets. Vomiting did not result in permanent treatment discontinuation [see Adverse Reactions (6.1)].

The safety and efficacy of Fexinidazole Tablets have not been established in pediatric patients younger than 6 years old and/or less than 20 kg in body weight.

8.5 Geriatric Use

Of the 619 subjects in the three clinical trials treated with Fexinidazole Tablets for HAT, there were 11 subjects who were 65 years of age or older, and no subjects greater than 75 years of age. There were an insufficient number of elderly subjects to detect differences in safety and/or effectiveness between elderly and younger adult patients.

8.6 Renal Impairment

No dosage adjustment is needed for patients with mild to moderate renal impairment with estimated glomerular filtration rates (eGFR) from 30 mL/min/1.73 m^2 to less than or equal to 89 mL/min/1.73 m^2 [see Clinical Pharmacology (12.3)]. The pharmacokinetics of fexinidazole in patients with severe renal impairment (eGFR less than 30 mL/min/1.73 m^2) is unknown. Avoid the use of Fexinidazole Tablets in patients with severe renal impairment.

8.7 Hepatic Impairment

No dosage adjustment of Fexinidazole Tablets is recommended for patients with mild hepatic impairment (Child-Pugh Class A). Moderate hepatic impairment (Child-Pugh Class B) increases fexinidazole and its active metabolite M1 exposures, which may increase the risk of adverse reactions [see Clinical Pharmacology (12.3)]. Use of Fexinidazole Tablets is contraindicated in patients with severe hepatic impairment [see Contraindications (4) and Warnings and Precautions (5.5)].

10 OVERDOSAGE

Randomized, controlled clinical studies were conducted in normal adult male subjects who were administered single or multiple oral doses of fexinidazole of up to 3,600 mg daily for 14 days (not an approved dose). The subjects experienced adverse reactions of increased transaminases, vomiting and panic attack [see Adverse Reactions (6.1)].

Reported symptoms of overdosage in a pediatric HAT patient following ingestion of a higher than recommended dosing regimen in Trial 3 included vomiting over the first 5 days of treatment and increased potassium and decreased calcium levels from Day 11 to Week 9.

There is no specific antidote for Fexinidazole Tablets. Treatment should be supportive with appropriate monitoring.

11 DESCRIPTION

Fexinidazole Tablets contain fexinidazole, a nitroimidazole antimicrobial drug for oral use.

The chemical name of fexinidazole is 1-methyl-2-{[4-(methylthio)phenoxy]methyl}-5-nitro-1H-imidazole.

Its molecular formula is C12H13N3O3S and the molecular weight is 279.3 g/mol. The structural formula is:

Fexinidazole is a yellow powder. It is practically insoluble in water, sparingly soluble in acetone and acetonitrile, very slightly soluble in ethanol and slightly soluble in methanol.

Fexinidazole 600 mg Tablets contain the active ingredient fexinidazole and the following inactive ingredients: croscarmellose sodium, lactose monohydrate, magnesium stearate, microcrystalline cellulose, povidone, and sodium lauryl sulfate.

12 CLINICAL PHARMACOLOGY

12.1 Mechanism of Action

Fexinidazole is an antiprotozoal drug [see Microbiology (12.4)].

12.2 Pharmacodynamics

Cardiac Electrophysiology

Concentration-dependent QTcF prolongation was observed with administration of Fexinidazole Tablets. Based on the exposure-response relationship, the mean (upper 90% confidence interval) increase in QTcF is predicted to be 19.0 msec (23.3 msec) at the recommended dosing regimen. The observed increase in QTcF appears to be associated with the M2 (sulfone) metabolite of fexinidazole [see Warning and Precautions (5.2)].

12.3 Pharmacokinetics

The pharmacokinetics (PK) of fexinidazole and its two pharmacologically active M1 (sulfoxide) and M2 (sulfone) metabolites following administration of the recommended adult dosage regimen of Fexinidazole Tablets in 12 healthy adult male subjects under fed conditions are presented in Table 5.

Table 5: Pharmacokinetics of Fexinidazole and its Active M1 and M2 Metabolites following Administration of Fexinidazole Tablets 1,800 mg Once Daily for 4 Days, Then 1,200 mg Once Daily for 6 Days to Healthy Adult Subjects Under Fed Conditions (N=12)
 |  | Fexinidazole | M1 | M2
Mean (±SD) Cmax mcg/mL | Day 1 | 1.6 (±0.4) | 8.1 (±2.2) | 7.5 (±3.3)
Mean (±SD) Cmax mcg/mL | Day 4 | 0.8 (±0.3) | 8.0 (±2.3) | 19.6 (±5.4)
Mean (±SD) Cmax mcg/mL | Day 10 | 0.5 (±0.2) | 5.9 (±2.1) | 12.5 (±3.5)
Mean (±SD) AUC(0–24 hours) mcg∙h/mL | Day 1 | 14.3 (±2.6) | 102.3 (±28.5) | 110.1 (±41.1)
Mean (±SD) AUC(0–24 hours) mcg∙h/mL | Day 4 | 11.6 (±2.2) | 127.9 (±49.2) | 391.5 (±126.7)
Mean (±SD) AUC(0–24 hours) mcg∙h/mL | Day 10 | 7.0 (±2.5) | 84.2 (±36.3) | 252.4 (±73.6)
Absorption
Median Tmax (Range) on Day 4, hours |  | 4 (0–9) | 4 (0–6) | 6 (0–24)
Effect of Food [The effect of food following administration of a single 1,200 mg dose with a meal containing approximately 963 Kcal with 62% of total calories from fat, 17% from protein, and 21% from carbohydrate (n=12).] |  | The AUC of fexinidazole, M1, and M2 were approximately 4 to 5-fold higher following administration with food compared to the fasted state.
Distribution
Apparent Volume of Distribution on Day 4, L |  | 3222 (±1199) | NA | NA
Plasma Protein Binding |  | 98% | 41% | 57%
Mean (Range) CSF concentrations at 24 hours after the last fexinidazole dose on Day 10, mcg/mL [From study in patient with HAT.] |  | NA | 1.39 (0–4.5) | 6.45 (0.3–14.9)
Mean (Range) CSF to DBS Ratios |  | NA | 0.53 (0.1–2.2) | 0.36 (0.1–0.8)
Elimination
Mean (±SD) Day 10 Half-life, hours |  | 15 (±6) | 16 (±6) | 23 (±4)
Mean (±SD) Apparent Clearance on Day 4, L/hour |  | 161 (±37) | NA | NA
Metabolism
Fexinidazole |  | - Fexinidazole is metabolized to M1 by several CYP450 enzymes, including CYP3A4 and flavin monooxygenases.
Active Metabolites |  | - Several CYP450 enzymes including, CYP3A4 and flavin monooxygenases, are involved in the metabolism of M1 to M2. - M2 is not further metabolized. - The AUC0–24 of M1 and M2 are 11 and 34-fold higher, respectively, than that of fexinidazole.
Excretion
Urine |  | Less than 3.2% of a given dose of Fexinidazole Tablets, primarily as M1 and M2 metabolites
Cmax = maximum plasma concentration; Tmax = time to maximum concentration; CSF = cerebrospinal fluid; CYP = cytochrome P450 enzymes; AUC0–24 hours = area under the plasma concentration-time curve from time zero to 24 hours, AUC0–t = area under the plasma concentration-time curve from time zero to the last timepoint with measurable analyte concentrations; DBS = dried blood spot
NA: Not available or not applicable

Specific Populations

Elderly patients

No specific pharmacokinetic studies have been performed in patients older than 65 years of age. In a population PK analysis of patients with HAT over a range of ages from 6 to 71 years, age was not a significant covariate affecting the PK of fexinidazole and the M1 and M2 metabolites and no differences in the PK of any of these three moieties were observed.

Pediatric patients

The ranges of plasma AUC values of fexinidazole, M1, and M2 in pediatric and adult HAT patients with body weights greater than or equal to 20 kg were overlapping following administration of Fexinidazole Tablets at the recommended pediatric and adult dosage regimens, indicating similar systemic exposures across body weights of 20 kg and greater.

Hepatic impairment

Following a single 1200 mg dose of Fexinidazole Tablets to subjects with mild hepatic impairment (Child-Pugh A; n=7), fexinidazole, M1 and M2 AUC estimates were 1.40-fold higher, 1.13-fold higher, and 1.20-fold higher, respectively, and their half-life estimates were 1.38-fold higher, 1.18-fold higher, and 0.93-fold lower, respectively. Sum of AUCs of active metabolites M1 and M2 was increased by 5%, in comparison to subjects without hepatic impairment (n=7).

In the same study, in subjects with moderate hepatic impairment (Child-Pugh Class B, n=7), fexinidazole, M1 and M2 AUC estimates were 1.36-fold higher, 1.46-fold higher, and 0.65-fold lower, respectively, and their half-life estimates were 1.77-fold higher, 1.25-fold higher, and 1.34-fold higher, respectively. Sum of AUCs of active metabolites M1 and M2 was decreased by 18%, compared to subjects without hepatic impairment (n=7).

The unbound fraction of fexinidazole was not affected by mild or moderate hepatic impairment. The effect of severe hepatic impairment (Child-Pugh class C) on fexinidazole pharmacokinetics is unknown. [see Contraindications (4) and Use in Specific Populations (8.7)].

Renal Impairment

A population PK analysis, based on baseline renal function, was carried out with data from 317 HAT patients enrolled in clinical trials that included 212 patients with normal renal function (eGFR greater than or equal to 90 mL/min/1.73 m^2), 89 patients with mild renal impairment (eGFR 60 to less than 90 mL/min/1.73 m^2), and 14 patients with moderate renal impairment (eGFR 30 to less than 60 mL/min/1.73 m^2). The predicted AUC0–24 estimates for fexinidazole and its M1 and M2 metabolites were similar in patients with mild or moderate renal impairment compared to those patients without renal impairment. The PK of fexinidazole in patients with severe renal impairment has not been studied [see Use in Specific Populations (8.6)].

Race/ethnicity

Insufficient data were available from the clinical trials to assess the effect of race or ethnicity on fexinidazole PK.

Drug Interaction Studies

In vitro studies

Cytochrome P450 (CYP450) and UDP-glucuronosyl transferase (UGT) Enzymes: Fexinidazole has the potential to inhibit CYP1A2, CYP2B6, CYP2C19, CYP2D6, and CYP3A4/5; M1 has the potential to inhibit CYP2C19; M2 does not inhibit any CYPs.

Fexinidazole has the potential to induce CYP1A2 and CYP2B6. Metabolite M1 has the potential to induce CYP1A2, CYP2B6, CYP3A5, UGT1A4, UGT2B4 and UGT2B7. Metabolite M2 has the potential to induce UGT2B4 [see Drug Interactions (7.2)].

Transporter Systems: Fexinidazole inhibits OATP1B1, OATP1B3, OCT2, OAT1, OAT3, MATE1 and MATE2-K transporters. M1 inhibits OAT3, MATE1, and MATE2-K. M2 inhibits OCT2, OAT1, OAT3, MATE1, and MATE2-K. Coadministration with Fexinidazole Tablets may increase the plasma concentrations of drugs that are substrates of these aforementioned transporters [see Drug Interactions (7.2)]. Fexinidazole, M1, or M2 do not inhibit P-gp or BCRP.

Clinical studies

A clinical drug-drug interaction study evaluated the effect of fexinidazole following administration of 1,800 mg Fexinidazole Tablets for four days, followed by 1,200 mg on Day 5, with single dose administration of 100 mg caffeine (probe substrate of CYP1A2) and 20 mg omeprazole (probe substrate of CYP2C19) on Day 4 in healthy subjects. The mean caffeine AUC was 2-fold higher, with no significant increase in Cmax compared to when caffeine was administered alone. The mean Cmax and AUC of omeprazole were approximately 2-fold higher compared to when omeprazole was administered alone [see Drug Interactions (7.2)].

A clinical drug-drug interaction study evaluated the effect of fexinidazole following administration of 1,800 mg Fexinidazole Tablets for four days, followed by 1,200 mg on Day 5 (not an approved dosing regimen), with single dose administration of 2 mg midazolam (probe substrate of CYP3A4/5) on Day 4 in healthy subjects. The mean midazolam AUC was decreased by 57%, mean Cmax by 39% and mean half-life by 33% compared to when midazolam was administered alone [see Drug Interactions (7.2)].

Model-informed approaches

Findings from a static mechanistic model-based analysis predicted that fexinidazole may decrease the systemic PK exposure of CYP2B6 substrates [see Drug Interactions (7.2)].

This model-based analysis predicted no significant drug interaction of fexinidazole with drugs that are substrates of CYP2C8, CYP2C9, or CYP2D6.

12.4 Microbiology

Mechanism of Action

Studies with Trypanosoma brucei and other protozoans suggest that, like for other nitro-containing drugs, the nitroreductase (NTR) enzyme plays an important role in the bioactivation of fexinidazole resulting in generation of reactive amines and damage to DNA and proteins. The activity of fexinidazole and its metabolites (M1 and M2) is trypanocidal and appears to be concentration and time dependent. However, the precise mechanism by which fexinidazole and the two metabolites exhibit activity against T. brucei is not known.

Antimicrobial Activity

Fexinidazole and its two metabolites, M1 and M2, are active against the trypanosomes of Trypanosoma brucei gambiense.

Resistance

In vitro studies suggest a potential for development of resistance in T. brucei against fexinidazole.

The mechanism of resistance appears to be similar to other nitro-containing drugs, such as nifurtimox, and include down-regulation of Type 1 NTR. However, the clinical relevance of these findings is not known.

Cross-Resistance

Nonclinical studies suggest cross-resistance between fexinidazole and other nitro-containing drugs such as nifurtimox. This appears to be due to down regulation of Type I NTR. Although the clinical relevance of these findings is not known, the potential for the development of resistance to fexinidazole in patients previously treated with nifurtimox-eflornithine combination therapy (NECT) cannot be discounted.

13 NONCLINICAL TOXICOLOGY

13.1 Carcinogenesis, Mutagenesis, Impairment of Fertility

Carcinogenicity

No carcinogenicity study was performed with fexinidazole.

Carcinogenicity has been observed in mice and rats treated chronically with nitroimidazole-class drugs which are structurally similar to fexinidazole. It is unclear if the findings of tumors in lifetime rodent studies indicate a risk to patients taking a 10-day treatment of Fexinidazole Tablets for HAT.

Mutagenesis

Fexinidazole and the M2 metabolite were mutagenic in the Ames test. Fexinidazole was negative in the in vitro micronucleus test in cultured human peripheral blood lymphocytes, the rat liver unscheduled DNA synthesis (UDS) assay, and the in vivo mouse micronucleus assay.

Impairment of Fertility

In the fertility and early embryonic development study, male rats were treated for 28 days prior to start of cohabitation with treated females and throughout the cohabitation period until sacrifice. Female rats were treated for 14 days prior to start of cohabitation with treated males throughout the cohabitation period until copulation occurred and up to GD 7. Fexinidazole showed no effect on fertility parameters and no evidence of impairment of reproductive performance up to the dose of 600 mg/kg/day (estimated to be approximately 1.03 times the clinical exposure based on AUC comparisons).

14 CLINICAL STUDIES

Trial 1

The efficacy and safety of Fexinidazole Tablets were evaluated in a randomized, comparative open-label trial (Trial 1, NCT01685827) conducted in adult patients with late second-stage HAT due to T. brucei gambiense. Patients had evidence of parasites in blood, lymph and/or cerebrospinal fluid (CSF) at trial enrollment. If testing for parasites in CSF was negative, a CSF WBC >20 cells/μL was required to confirm late second-stage HAT. Patients (n=394) were randomized in a 2:1 ratio to a 10-day treatment regimen of either Fexinidazole Tablets (n=264) or nifurtimox-eflornithine combination therapy (NECT) (n=130). The mean age was 35 years (range 15 to 71) and 61% were male. The fexinidazole tablet group received 1,800 mg of Fexinidazole Tablets orally once daily on Days 1 through 4, followed by 1,200 mg orally once daily on Days 5 through 10, with all dosing in the fed state. The NECT control arm received nifurtimox tablets 15 mg/kg/day in three divided doses for 10 days as well as eflornithine injectable solution 400 mg/kg/day in two divided doses for 7 days. Patients were hospitalized throughout their treatment and were allowed to leave the hospital from Day 13 onwards if their clinical status was satisfactory. Patients were followed up at 3, 6, 12, 18, and 24 months after the end of treatment visit. HAT symptoms reported at baseline in >50% of patients included headache, pruritus, sleepiness, weight loss, and asthenia. The median CSF WBC count was 157 cells/µL.

The outcome at 18 months was considered a success if patients were classified as a cure or probable cure as defined below:

- Cure: Patient is alive with no evidence of trypanosomes in any body fluid and CSF WBC ≤20 cells/µL.
- Probable cure for patients who refused a lumbar puncture (or who had a hemorrhagic CSF sample) at 18 months: No parasites in the blood or lymph and a satisfactory clinical condition without clinical signs or symptoms (or clinical status is unlikely to be due to HAT), CSF WBC <50 cells/µL at 6 and/or 12 months and not increasing at 12 months, as long as there was no indication of a relapse up to 24 months and no definitive failure (presence of trypanosomes) had been observed before in any body fluid.

Success rates at 18 months are shown in Table 6 for the modified intention-to-treat (mITT) population, which consisted of all randomized patients who received at least one dose of study treatment but excluded 5 randomized patients due to geopolitical unrest. The success rate in the fexinidazole treatment arm was lower than in the NECT arm. Additionally, more deaths occurred in the fexinidazole treatment arm at 24 months (n=9, 3.4%) compared to the NECT treatment arm (n=2, 1.6%). This decreased efficacy and increased mortality was noted in the subgroup of patients who had CSF-WBC >100 cells/µL at baseline [see Warnings and Precautions (5.1)]. The results at 24 months were consistent with the results at 18 months with 24-month success rates of 89.7% (235/262) in the fexinidazole treatment arm and 97.6% (124/127) in the NECT arm.

Table 6: Success Rates at 18 Months (mITT population) in Trial 1
 | Fexinidazole | NECT | Difference (97% CI [Analysis adjusted for interim analysis to control the overall Type I error at two-sided 0.05.])
N | 262 | 127 | –
Success at 18 months [Two fexinidazole treated patients were considered as failures due to loss to follow-up and consent withdrawal prior to 18 months.] | 239 (91.2%) | 124 (97.6%) | -6.4% (-11.6%, -0.1%)
Success at 18 months by baseline CSF-WBC [CSF-WBC represents white blood cell count in cerebrospinal fluid at baseline.]
Baseline CSF-WBC ≤100 cells/µL | 100/102 (98.0%) | 47/49 (95.9%) | –
Baseline CSF-WBC >100 cells/µL | 139/160 (86.9%) | 77/78 (98.7%) | –

Trial 2 and Trial 3

Additional supportive evidence for efficacy in early stage HAT due to T. brucei gambiense, and in pediatric patients was obtained from two single-arm trials: a single-arm trial in adults (Trial 2, NCT02169557), and a single-arm trial in pediatric patients aged 6 to 15 years old and weighing at least 20 kg (Trial 3, NCT02184689). In Trial 2, the mean age of patients was 34 years and 82% of patients had evidence of first-stage HAT (evidence of trypanosomes in the blood or lymph, no trypanosomes in the CSF, and CSF WBC ≤5 cells /µL). In Trial 3, the mean age of patients was 11 years and 55% of patients had evidence of first-stage HAT. Fexinidazole Tablets 1,200 mg, was given in fed condition once a day on Days 1 through 4, followed by 600 mg on Days 5 through 10 to patients weighing <35 kg, and all other patients received the adult dosing regimen. Treatment success proportions in all patients with first- or late-stage HAT were 98.7% (227/230, 95% CI [96.2%, 99.7%]) at 12 months in Trial 2 and 97.6% (122/125, 95% CI [93.1%, 99.5%]) at 12 months in Trial 3. The results at 18 months were consistent with the results at 12 months.

16 HOW SUPPLIED/STORAGE AND HANDLING

Fexinidazole 600 mg tablets are pale-yellow, round, biconvex tablets debossed with "4512" on one side.

Fexinidazole 600 mg tablets are supplied as:

- NDC 0024-4512-24, child-resistant blister pack of 24 tablets (10-day dose pack) for adults and pediatric patients weighing 35 kg or more.
- NDC 0024-4512-14, child-resistant blister pack of 14 tablets (10-day dose pack) for pediatric patients older than 6 years weighing 20 kg to less than 35 kg.

STORAGE AND HANDLING

Store below 30°C (86°F). Store in the original package in order to protect from light and moisture.

17 PATIENT COUNSELING INFORMATION

Administration with Food

Advise the patient that Fexinidazole Tablets must be taken with food each day at about the same time of the day (e.g., during or immediately after the main meal of the day), to make sure it is adequately absorbed [see Dosage and Administration (2.1, 2.2)].

Alcohol Consumption

Advise patients not to consume alcoholic beverages during treatment with Fexinidazole Tablets and for at least 48 hours after completing Fexinidazole Tablets therapy [see Dosage and Administration (2.1) and Warnings and Precautions (5.6)].

Vomiting

Advise the patient not to administer an additional dose if vomiting occurs after the administration of Fexinidazole Tablets but continue with the next scheduled dose the following day. If a second event of vomiting occurs after administration of any other dose of Fexinidazole Tablets, counsel the patient on the importance of contacting the healthcare provider immediately [see Dosage and Administration (2.1)].

Missed Doses

Advise patients that if a scheduled dose is missed (not taken on the assigned day), normal dosing should resume the following day until the full course (10 days) of treatment has been completed. Counsel the patient on the importance of contacting the health care practitioner immediately if a second scheduled dose is missed [see Dosage and Administration (2.1)].

Neuropsychiatric Adverse Reactions

Counsel patients and their caregivers of the risk for neuropsychiatric adverse reactions, such as insomnia, headache, tremor, mood changes, psychiatric disorders (such as agitation, anxiety, abnormal behavior, depression, nightmares, hallucination, and personality change) and suicidal ideation [see Warnings and Precautions (5.3) and Adverse Reactions (6.1)]. If such adverse reactions occur, advise the patients and their caregivers to contact their healthcare provider immediately.

Dizziness

Counsel the patient that they should not drive or use machines if they feel tired or dizzy. Dizziness, fatigue, asthenia, and somnolence have been reported following treatment with Fexinidazole Tablets [see Adverse Reactions (6.1)].

Drug Interactions

Advise patients to disclose to their healthcare provider all other medications, including herbal medicines, the patient is currently taking while being treated with fexinidazole tablets [see Drug Interactions (7)].

Manufactured by:
sanofi-aventis U.S. LLC
Morristown, NJ 07960
A SANOFI COMPANY
©2025 sanofi-aventis U.S. LLC

PRINCIPAL DISPLAY PANEL - 600 mg Tablet Dose Pack

Opening Instructions:
Press and hold down
button while pulling out
medication card.

NDC 0024-4512-24
Rx only

Fexinidazole
Tablets

600 mg per tablet

10-Day Dose Pack
for adults and children
weighing 35 kg or more

DISPENSE ONLY IN ORIGINAL PACKAGE

24 tablets
SANOFI